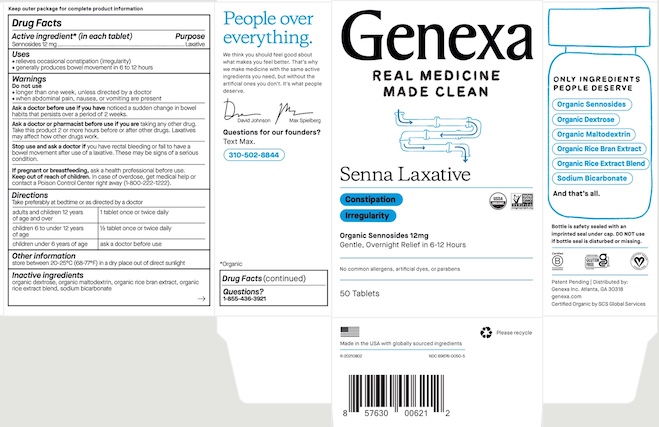 DRUG LABEL: Genexa Senna Laxative
NDC: 69676-0050 | Form: TABLET
Manufacturer: Genexa Inc.
Category: otc | Type: HUMAN OTC DRUG LABEL
Date: 20220724

ACTIVE INGREDIENTS: SENNOSIDES 12 mg/1 1
INACTIVE INGREDIENTS: BROWN RICE; SODIUM BICARBONATE; DEXTROSE; MALTODEXTRIN; RICE BRAN

Senna Laxative

Keep outer package for complete product information

Drug Facts

Active ingredient* (in each tablet)

Sennosides 12 mg

Purpose

Laxative

Uses

- relieves occasional constipation (irregularity)
- generally produces bowel movement in 6 to 12 hours

Warnings

Do not use

- longer than one week, unless directed by a doctor
- when abdominal pain, nausea, or vomiting are present

Ask a doctor before use if you have noticed a sudden change in bowel habits that persists over a period of 2 weeks.

Ask a doctor or pharmacist before use if you are taking any other drug. Take this product 2 or more hours before or after other drugs. Laxatives may affect how other drugs work.

Stop use and ask a doctor if you have rectal bleeding or fail to have a bowel movement after use of a laxative. These may be signs of a serious conditon.

PREGNANCY OR BREAST FEEDING

If pregnant or breastfeeding, ask a health professional before use.

Keep out of reach of children. In case of overdose, get medical help or contact a Poison Control Center right away.

Directions

Take preferably at bedtime or as directed by a doctor.

adults and children 12 years of age and over | 1 tablet once or twice daily
children 6 to under 12 years of age | 1/2 tablet once or twice daily
children under 6 years of age | ask a doctor before use

Other information

store between 20-25°C (68-77°F) in a dry place out of direct sunlight

INACTIVE INGREDIENT

Inactive ingredients organic dextrose, organic maltodextrin, organic rice bran extract, organic rice extract blend, sodium bicarbonate.

Questions?

1-855-436-3921

*Organic

Bottle is safety sealed with an imprinted seal under cap. DO NOT use if bottle seal is disturbed or missing.

Patent Pending | Distributed by:

Genexa Inc. Los Angeles, CA 90034

genexa.com

Certified Organic by SCS Global Services

Made in the USA with globally sourced ingredients

R-20210802

NDC 69676-0050-5

PACKAGE LABEL

Genexa

REAL MEDICINE MADE CLEAN

Senna Laxative

Constipation

Irregularity

Organic Sennosides 12mg

Gentle, Overnight Relief in 6-12 Hours

No common allergens, dyes, or parabens

50 Tablets